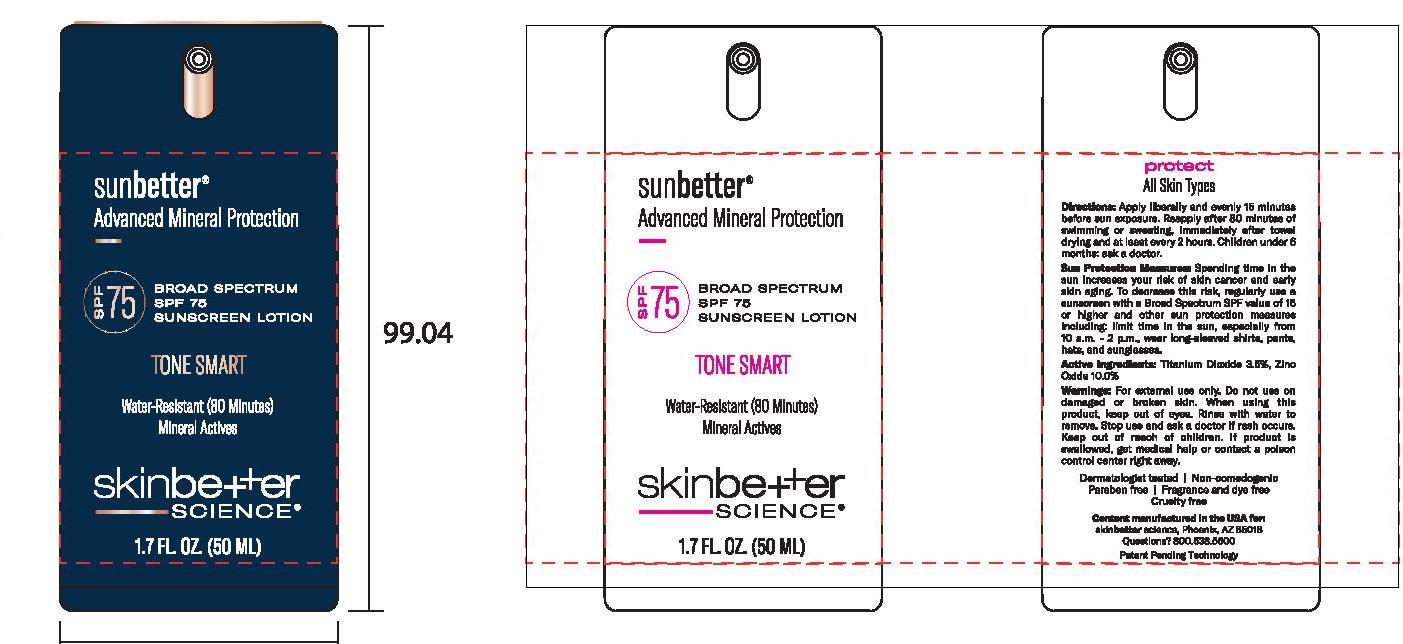 DRUG LABEL: sunbetter Broad Spectrum SPF 75 Sunscreen Tone Smart
NDC: 73291-0003 | Form: LOTION
Manufacturer: SKINBETTER SCIENCE LLC
Category: otc | Type: HUMAN OTC DRUG LABEL
Date: 20250106

ACTIVE INGREDIENTS: TITANIUM DIOXIDE 35 mg/1 mL; ZINC OXIDE 100 mg/1 mL
INACTIVE INGREDIENTS: SODIUM BENZOATE; SODIUM CHLORIDE; STYRENE/ACRYLAMIDE COPOLYMER (500000 MW); .ALPHA.-TOCOPHEROL ACETATE, DL-; GINGER; ALLANTOIN; ALUMINUM OXIDE; MEDIUM-CHAIN TRIGLYCERIDES; CAPRYLYL GLYCOL; STARCH, CORN; TRIETHYL CITRATE; UBIDECARENONE; WATER; SILICON DIOXIDE; DODECAMETHYLPENTASILOXANE; OPUNTIA FICUS-INDICA STEM; PHENYLETHYL ALCOHOL; PHENOXYETHANOL; POLY(METHYL METHACRYLATE; 450000 MW); SQUALANE; STEARIC ACID; CAPER BERRY; CETYL DIMETHICONE 45; .ALPHA.-BISABOLOL, (+/-)-; BUTYLOCTYL SALICYLATE; CAMELLIA OLEIFERA LEAF; CERIC OXIDE; DISTEARDIMONIUM HECTORITE; HIMANTHALIA ELONGATA; MICA; NIACINAMIDE; DIMETHICONE; GLYCERIN; FERRIC OXIDE RED; BLACK OLIVE; OLEA EUROPAEA LEAF; PANTHENOL; PHENYL TRIMETHICONE; POLYGLYCERYL-4 OLEATE; POLYGONUM AVICULARE TOP; POLYHYDROXYSTEARIC ACID (2300 MW); POTASSIUM SORBATE; 1,2-HEXANEDIOL; TROPOLONE

sunbetter TONE SMART SPF 75 Sunscreen Lotion

Drug Facts

Active Ingredients

Titanium Dioxide 3.5%

Zinc Oxide 10.0%

Purpose

Sunscreen

Uses

Helps prevent sunburn.

If used as directed with other sun protection measures (see Directions), decreases the risk of skin cancer and early skin aging caused by the sun.

Warnings

For external use only.

Do not use on damaged or broken skin.

When using this product keep out of eyes. Rinse with water to remove.

Stop use and ask a doctor if rash occurs.

Keep out of reach of children. If swallowed, get medical help or contact a Poison Control Center right away.

Directions

Sun Protection Measures: Spending time in the sun increases your risk of skin cancer and early skin aging. To decrease this risk, regularly use a sunscreen with a Broad Spectrum SPF value of 15 or higher and other sun protection measures including:

limit time in the sun, especially from 10 a.m. - 2 p.m.

wear long-sleeved shirts, pants, hats and sunglasses.

Children under 6 months of age: Ask a doctor.

DOSAGE AND ADMINISTRATION

Apply liberally and evenly 15 minutes before sun exposure.

Reapply:

after 80 minutes of swimming or sweating.

immediately after towel drying.

at least every 2 hours.

use a water resistant sunscreen if swimming or sweating.

Inactive ingredients

1,2-Hexanediol, Acrylates/Dimethicone Copolymer, Allantoin, Alumina, Bis-Vinyl Dimethicone/Dimethicone Copolymer, Bisabolol, Butyloctyl Salicylate, Camellia Oleifera Leaf Extract, Capparis Spinosa Fruit Extract, Caprylic/Capric Triglyceride, Caprylyl Glycol, Cerium Oxide, Cetyl Dimethicone, Dimethicone, Disteardimonium Hectorite, Glycerin, Himanthalia Elongata Extract, Iron Oxides (CI 77491, CI 77492, CI 77499), Mica, Niacinamide, Olea Europaea (Olive) Fruit Extract, Olea Europaea (Olive) Leaf Extract, Opuntia Ficus-Indica Stem Extract, Panthenol, Phenethyl Alcohol, Phenoxyethanol, Phenyl Trimethicone, Plankton Extract, Polyglyceryl-3 Sorbityl Linseedate, Polyglyceryl-4 Oleate, Polygonum Aviculare Extract, Polyhydroxystearic Acid, Polymethyl Methacrylate, Potassium Sorbate, Silica, Sodium Benzoate, Sodium Chloride, Squalane, Stearic Acid, Styrene/Acrylates Copolymer, Tocopheryl Acetate, Triethyl Citrate, Tropolone, Ubiquinone, Water, Zea Mays (Corn) Starch, Zingiber Officinale (Ginger) Root Extract.

Other information

Protect this product from excessive heat and direct sun.

Questions or comments?

800-538-5600

Principal Display Panel

sunbetter™

Advanced Mineral Protection

BROAD SPECTRUM SPF 75

SUNSCREEN LOTION

TONE SMART

Water-Resistant (80 Minutes)

Mineral Actives

skinbetter science®

1.7 FL.OZ. (50 ML)